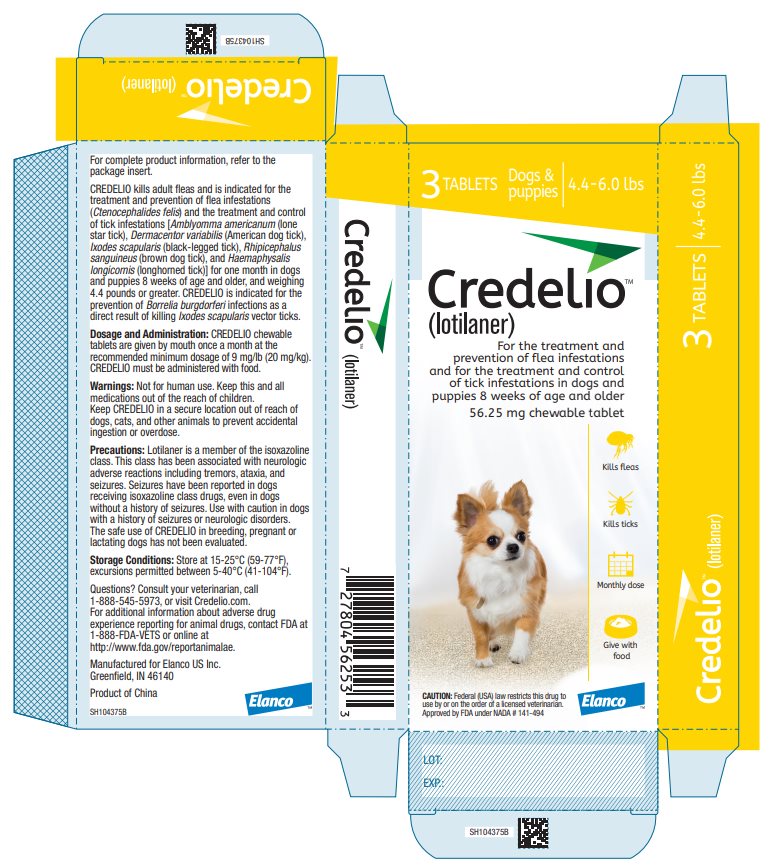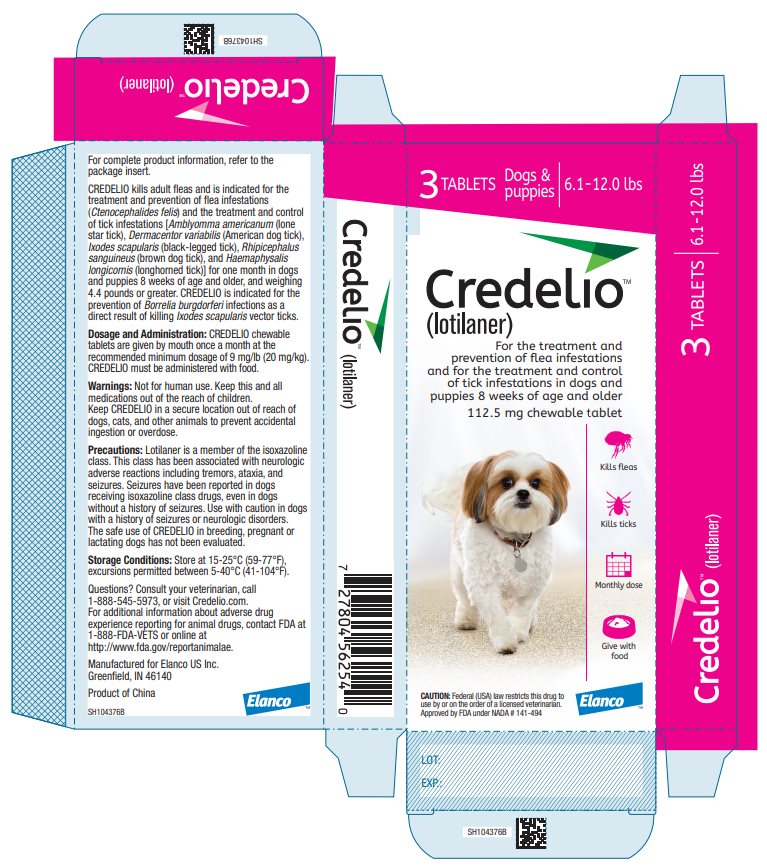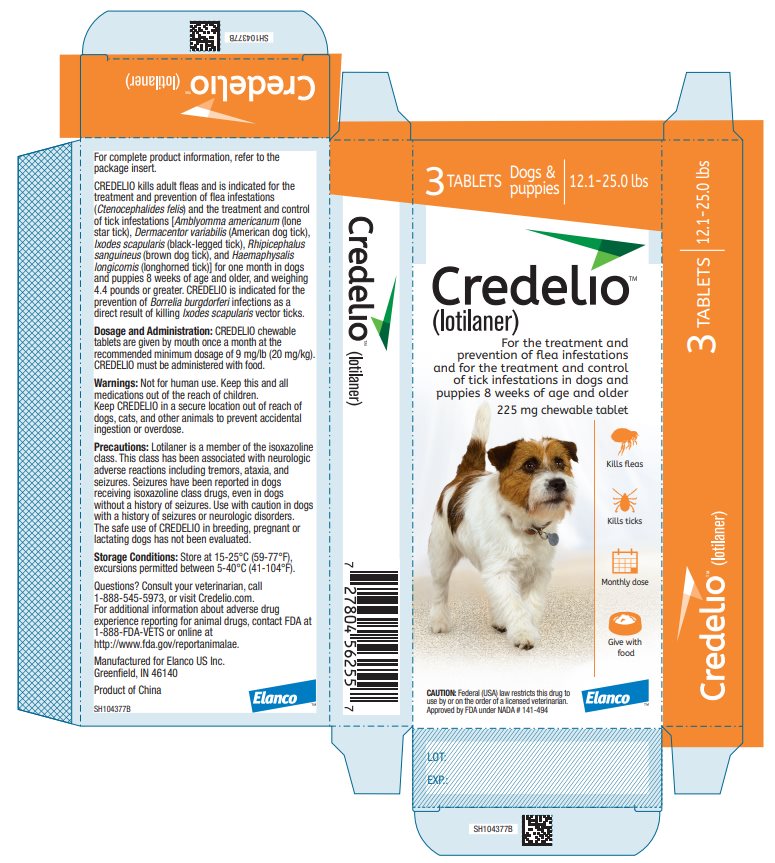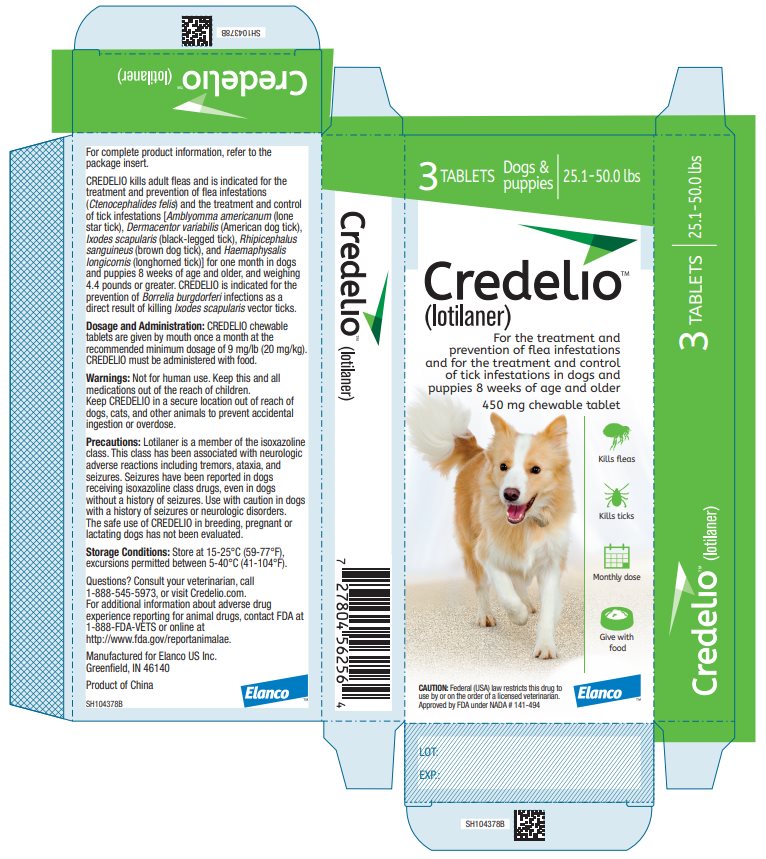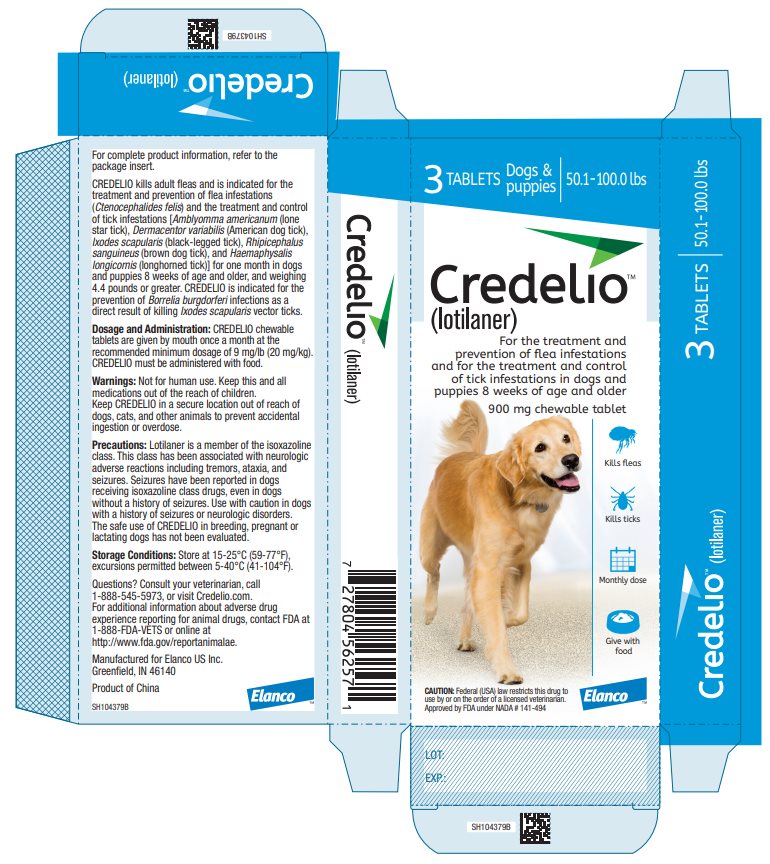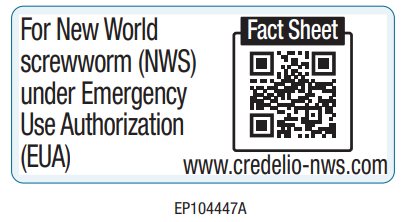 DRUG LABEL: Credelio
NDC: 58198-5452 | Form: TABLET, CHEWABLE
Manufacturer: Elanco US Inc.
Category: animal | Type: PRESCRIPTION ANIMAL DRUG LABEL
Date: 20260220

ACTIVE INGREDIENTS: Lotilaner 56.25 mg/1 1

Credelio™
(lotilaner)

Chewable Tablets

For oral use in dogs

Caution:

Federal law restricts this drug to use by or on the order of a licensed veterinarian.

Description:

CREDELIO (lotilaner) is a beef-flavored, chewable tablet for oral administration to dogs and puppies according to their weight. Each chewable tablet is formulated to provide a minimum lotilaner dosage of 9 mg/lb (20 mg/kg).

Lotilaner has the chemical composition of 5-[(5S)-4,5-dihydro-5-(3,4,5-trichlorophenyl)-5-(trifluoromethyl)-3-isoxazolyl]-3-methyl-N-[2-oxo-2-[(2,2,2-trifluoroethyl)amino]ethyl]-2-thiophenecarboxamide.

Indications:

CREDELIO kills adult fleas and is indicated for the treatment and prevention of flea infestations (Ctenocephalides felis) and the treatment and control of tick infestations [Amblyomma americanum (lone star tick), Dermacentor variabilis (American dog tick), Ixodes scapularis (black-legged tick), Rhipicephalus sanguineus (brown dog tick), and Haemaphysalis longicornis (longhorned tick)] for one month in dogs and puppies 8 weeks of age and older, and weighing 4.4 pounds or greater. CREDELIO is indicated for the prevention of Borrelia burgdorferi infections as a direct result of killing Ixodes scapularis vector ticks.

Dosage and Administration:

CREDELIO is given orally once a month, at the minimum dosage of 9 mg/lb (20 mg/kg).

Dosage Schedule:

Body Weight | Lotilaner Per Chewable Tablet (mg) | Chewable Tablets Administered
4.4 to 6.0 lbs | 56.25 | One
6.1 to 12.0 lbs | 112.5 | One
12.1 to 25.0 lbs | 225 | One
25.1 to 50.0 lbs | 450 | One
50.1 to 100.0 lbs | 900 | One
Over 100.0 lbs | Administer the appropriate combination of chewable tablets

CREDELIO must be administered with food (see Clinical Pharmacology).

Treatment with CREDELIO can begin at any time of the year and can continue year-round without interruption.

Contraindications:

There are no known contraindications for the use of CREDELIO.

Warnings:

Not for human use. Keep this and all drugs out of the reach of children. Keep CREDELIO in a secure location out of reach of dogs, cats, and other animals to prevent accidental ingestion or overdose.

Precautions:

Lotilaner is a member of the isoxazoline class. This class has been associated with neurologic adverse reactions including tremors, ataxia, and seizures. Seizures have been reported in dogs receiving isoxazoline class drugs, even in dogs without a history of seizures. Use with caution in dogs with a history of seizures or neurologic disorders.

The safe use of CREDELIO in breeding, pregnant or lactating dogs has not been evaluated.

Adverse Reactions:

In a well-controlled U.S. field study, which included 284 dogs (198 dogs treated with CREDELIO and 86 dogs treated with an oral active control), there were no serious adverse reactions.

Over the 90-day study period, all observations of potential adverse reactions were recorded. Reactions that occurred at an incidence of 1% or greater are presented in the following table.

Dogs with Adverse Reactions in the Field Study

Adverse Reaction (AR) | CREDELIO Group: Number (and Percent) of Dogs with the AR (n=198) | Active Control Group: Number (and Percent) of Dogs with the AR (n=86)
Weight Loss | 3 (1.5%) | 2 (2.3%)
Elevated Blood Urea Nitrogen (BUN) | 2 (1.0%)* | 0 (0.0%)
Polyuria | 2 (1.0%)* | 0 (0.0%)
Diarrhea | 2 (1.0%) | 2 (2.3%)
*Two geriatric dogs developed mildly elevated BUN (34 to 54 mg/dL; reference range: 6 to 31 mg/dL) during the study. One of these dogs also developed polyuria and a mildly elevated potassium (6.5 mEq/L; reference range: 3.6 to 5.5 mEq/L) and phosphorous (6.4 mg/dL; reference range: 2.5 to 6.0 mg/dL). The other dog also developed a mildly elevated creatinine (1.7 to 2.0 mg/dL; reference range: 0.5 to 1.6 mg/dL) and weight loss.

In addition, one dog experienced intermittent head tremors within 1.5 hours of administration of vaccines, an ear cleaning performed by the owner, and its first dose of CREDELIO. The head tremors resolved within 24 hours without treatment. The owner elected to withdraw the dog from the study.

In an Australian field study, one dog with a history of seizures experienced seizure activity (tremors and glazed eyes) six days after receiving CREDELIO. The dog recovered without treatment and completed the study. In the U.S. field study, two dogs with a history of seizures received CREDELIO and experienced no seizures throughout the study.

In three well-controlled European field studies and one U.S. laboratory study, seven dogs experienced episodes of vomiting and four dogs experienced episodes of diarrhea between 6 hours and 3 days after receiving CREDELIO.

Post-Approval Experience (2023):

The following adverse events are based on post-approval adverse drug experience reporting for CREDELIO. Not all adverse events are reported to FDA/CVM. It is not always possible to reliably estimate the adverse event frequency or establish a causal relationship to product exposure using these data.

The following adverse events reported in dogs are listed in decreasing order of reporting frequency:

Vomiting, diarrhea (with and without blood), lethargy, anorexia, seizure, pruritus, ataxia, urinary-related signs (polyuria, polydipsia, urinary incontinence, and inappropriate urination), and muscle tremor.

Contact Information:

To report suspected adverse events, for technical assistance or to obtain a copy of the Safety Data Sheet (SDS), contact Elanco US Inc. at 1-888-545-5973.

For additional information about adverse drug experience reporting for animal drugs, contact FDA at 1-888-FDA-VETS or http:/www.fda.gov/reportanimalae.

Clinical Pharmacology:

Following oral administration of 43 mg/kg (approximately 1X the maximum labeled dose), peak lotilaner concentrations were achieved between 6 hours and 3 days in dogs 2 months of age and between 1 and 7 days in dogs 10 months of age. Dogs 2 months of age had a shorter elimination half-life (average of 9.6 days) than at 10 months of age (average of 28.4 days). Due to reduced drug bioavailability in the fasted state, CREDELIO must be administered with a meal or within 30 minutes after feeding.

Mode of Action:

Lotilaner is an ectoparasiticide belonging to the isoxazoline group. Lotilaner inhibits insect and acarine gamma-aminobutyric acid (GABA)-gated chloride channels. This inhibition blocks the transfer of chloride ions across cell membranes, which results in uncontrolled neuromuscular activity leading to death of insects and acarines. The selective toxicity of lotilaner between insects and acarines and mammals may be inferred by the differential sensitivity of the insects and acarines' GABA receptors versus mammalian GABA receptors.

Effectiveness:

In well-controlled European laboratory studies, CREDELIO began to kill fleas four hours after administration or infestation, with greater than 99% of fleas killed within eight hours after administration or infestation for 35 days. In a well-controlled U.S. laboratory study, CREDELIO demonstrated 100% effectiveness against adult fleas 12 hours after administration or infestation for 35 days.

In a 90-day well-controlled U.S. field study conducted in households with existing flea infestations of varying severity, the effectiveness of CREDELIO against fleas on Days 30, 60 and 90 compared to baseline was 99.5%,100% and 100%, respectively. Dogs with signs of flea allergy dermatitis showed improvement in erythema, papules, scaling, alopecia, dermatitis/pyodermatitis and pruritus as a direct result of eliminating fleas.

In a well-controlled laboratory study, CREDELIO killed fleas before they could lay eggs, thus preventing subsequent flea infestations for 30 days after the start of treatment of existing flea infestations.

In well-controlled laboratory studies, CREDELIO demonstrated > 97% effectiveness against Amblyomma americanum, Dermacentor variabilis, Ixodes scapularis, Rhipicephalus sanguineus, and Haemaphysalis longicornis ticks 48 hours after administration or infestation for 30 days. In a well-controlled European laboratory study, CREDELIO started killing Ixodes ricinus ticks within four hours after administration.

In two separate, well-controlled laboratory studies, CREDELIO was effective at preventing Borrelia burgdorferi infections after dogs were infested with Ixodes scapularis vector ticks.

Palatability: In the U.S. field study, which included 567 doses administered to 198 dogs, 80.4% of dogs voluntarily consumed CREDELIO when offered by hand or in an empty bowl, an additional 13.6% consumed CREDELIO when offered with food, and 6.0% required placement of the chewable tablet in the back of the dog's mouth.

Animal Safety:

In a margin of safety study, CREDELIO was administered orally to 24 (8 dogs/group) 8-week-old Beagle puppies at doses of 43 mg/kg, 129 mg/kg, and 215 mg/kg (approximately 1, 3, and 5X the maximum labeled dose, respectively) every 28 days for eight consecutive doses. The 8 dogs in the control group (0X) were untreated. There were no clinically-relevant, treatment-related effects on clinical observations, physical and neurological examinations, body weights, food consumption, electrocardiograms, clinical pathology (hematology, clinical chemistries, coagulation profiles and urinalysis), gross pathology, histopathology, or organ weights. Blood concentrations of lotilaner confirmed systemic exposure of all treated dogs, although the exposure was less than dose proportional at 5X.

In a well-controlled field study, CREDELIO was used concurrently with other medications, such as vaccines, anthelmintics, antibiotics, steroids, NSAIDS, anesthetics, and antihistamines. No adverse reactions were observed from the concomitant use of CREDELIO with other medications.

Storage Information:

Store at 15-25°C (59 -77°F), excursions permitted between 5 to 40°C (41 to 104°F).

How Supplied:

CREDELIO is available in five chewable tablet sizes for use in dogs: 56.25, 112.5, 225, 450, and 900 mg lotilaner.

Each chewable tablet size is available in color-coded packages of 1, 3 or 6 chewable tablets.

Approved by FDA under NADA # 141-494

Manufactured for:
Elanco US Inc
Greenfield, IN 46140 USA
Credelio.com
Revised August 2025

Credelio, Elanco and the diagonal bar logo are trademarks of Elanco or its affiliates.
© 2025 Elanco or its affiliates

ElancoTM

PA104381X

Fact Sheet for Veterinarians: Emergency Use Authorization of Credelio™ (lotilaner)

Credelio™
(lotilaner)
Chewable Tablets
For oral use in dogs

Original EUA Authorized Date: 10/24/2025

Emergency Use Authorization for CREDELIO (lotilaner) for New World Screwworm (NWS)

The U.S. Food and Drug Administration (FDA) has issued an Emergency Use Authorization (EUA) for the emergency use of the approved product CREDELIO (lotilaner) for the treatment of infestations caused by NWS (Cochliomyia hominivorax) larvae (myiasis) in dogs and puppies. However, CREDELIO is not approved for this use.

CREDELIO is approved for other uses [On January 19, 2018, CREDELIO was approved to kill adult fleas and is indicated for the treatment and prevention of flea infestations (Ctenocephalides felis) and the treatment and control of tick infestations [Amblyomma americanum (lone star tick), Dermacentor variabilis (American dog tick), Ixodes scapularis (black-legged tick) and Rhipicephalus sanguineus (brown dog tick)] for one month in dogs and puppies 8 weeks of age and older, and weighing 4.4 pounds or greater. On September 3, 2019, CREDELIO received a supplemental approval for the prevention of flea infestations (Ctenocephalides felis) for one month in dogs and puppies 8 weeks of age and older, and weighing 4.4 pounds or greater. On October 24, 2025, CREDELIO received a supplemental approval for the treatment and control of Haemaphysalis longicornis (longhorned tick) tick infestations for one month in dogs and puppies 8 weeks of age and older, weighing 4.4 pounds or greater, and for the prevention of Borrelia burgdorferi infections as a direct result of killing Ixodes scapularis vector ticks.] .

Limitations of Authorized Use

CREDELIO (lotilaner) is authorized only for the duration of the declaration that circumstances exist justifying the authorization of the emergency use of CREDELIO (lotilaner) under section 564(b)(1) of the Federal Food, Drug, and Cosmetic Act (FD&C Act), 21 U.S.C. § 360bbb-3(b)(1), unless the authorization is terminated or revoked sooner.

Justification for Emergency Use of Animal Drugs for NWS

The Secretary of the U.S. Department of Health and Human Services (HHS) has:

- Determined that there is a significant potential for a public health emergency that has a significant potential to affect national security or the health and security of United States citizens living abroad and that involves NWS (Cochliomyia hominivorax) [https://public-inspection.federalregister.gov/2025-15918.pdf] .
- Declared “that circumstances exist justifying the authorization of emergency use of animal drugs to treat or prevent NWS myiasis in animals.”

An EUA is a FDA authorization for the emergency use of an unapproved product or unapproved use of an approved product (i.e., drug, biological product, or device) in the United States under certain circumstances including, but not limited to, when the Secretary of HHS declares circumstances exist justifying the product’s emergency authorization, based on a determination, including but not limited to a public health emergency or a significant potential for a public health emergency that may affect national security and that involves a biological agent [Emergency Use Authorization of Medical Products and Related Authorities | FDA (https://www.fda.gov/regulatoryinformation/search-fda-guidance-documents/emergency-use-authorization-medical-products-and-related-authorities)] . Criteria for issuing this EUA include:

- The biological agent can cause a serious or life-threatening disease or condition;
- Based on the available scientific evidence (including data from adequate and well-controlled clinical trials, if available), it is reasonable to believe that:
  - The product may be effective in diagnosing, treating or preventing the serious or life-threatening disease or condition; and
  - the known and potential benefits of the product - when used to treat such disease or condition - outweigh the known and potential risks of the product;
- There is no adequate, approved, and available alternative to the product for treating the serious or life-threatening disease or condition [https://www.fda.gov/emergency-preparedness-and-response/mcm-legal-regulatory-and-policy-framework/emergency-use-authorization] .

Caution: Federal law restricts this drug to use by or on the order of a licensed veterinarian.

Description:

Refer to the package insert for full Description information.

Dosage and Administration:

CREDELIO is given orally at the minimum dosage of 9 mg/lb (20 mg/kg).

Dosage Schedule:

Body Weight | Lotilaner Per Chewable Tablet (mg) | Chewable Tablets Administered
4.4 to 6.0 lbs | 56.25 | One
6.1 to 12.0 lbs | 112.5 | One
12.1 to 25.0 lbs | 225 | One
25.1 to 50.0 lbs | 450 | One
50.1 to 100.0 lbs | 900 | One
Over 100.0 lbs | Administer the appropriate combination of chewable tablets

CREDELIO must be administered with food.

CREDELIO is not available as scored tablets. The effectiveness of the administration of less than full tablets has not been evaluated.

Risk-Benefit Consideration for Dogs on Other Isoxazolines:

If a dog is currently receiving another isoxazoline product for routine ectoparasite control, veterinarians should consider administering CREDELIO to dogs diagnosed with NWS myiasis based on a risk-benefit assessment and the emergency nature of NWS myiasis treatment.

Information Supporting Emergency Use Authorization

Based on the scientific evidence available to FDA, including data from published scientific literature, it is reasonable to believe that CREDELIO may be effective for the treatment of infestations caused by NWS (Cochliomyia hominivorax) larvae (myiasis) in dogs and puppies; and the known and potential benefits of CREDELIO, outweigh the known and potential risks.

A study conducted by do Vale et al. [do Vale TL, Costa AR, Miranda LM, Silva GF, Silva NCS, Lima TB, Chaves DP, Sager H, Lasmar PVF, Costa-Junior LM. Efficacy of lotilaner against myiasis caused by Cochliomyia hominivorax (Diptera: Calliphoridae) in naturally infested dogs. Parasit Vectors. 2023;16(1):86.] evaluated the effectiveness of CREDELIO for the treatment of naturally acquired NWS myiasis in dogs in Brazil. Eleven client-owned dogs with active myiasis caused by C. hominivorax larvae were enrolled based on lesion severity and larval burden. The age of the enrolled dogs (5 males, 6 females) ranged from 1.5 to 10.0 years, weighing between 3.3 to 25.0 kg. All dogs received a single oral administration of CREDELIO at doses ranging from 23.9 to 40.9 mg/kg body weight, following the dose bands for the approved flea and tick indications. The study did not include a control group.

After treatment, the dogs were kept in individual kennels with a removable tray. The dogs were observed 2- and 6-hours post-treatment, at which times expelled larvae were collected and quantified. At 24 hours post-treatment, the remaining larvae were mechanically removed from the wound and counted.

The study demonstrated 100% overall effectiveness (number of expelled live and dead larvae and dead larvae mechanically removed) against C. hominivorax larvae at 24 hours posttreatment with expulsion of larvae of 80.5% and 93% at 2 and 6 hours after treatment, respectively. The mean larvicidal effectiveness was 41.1% at 24 hours. There were no adverse reactions during the study.

There are limitations of the data supporting the benefits of CREDELIO for the treatment of infestations caused by NWS larvae. The do Vale et al. study was conducted in a limited population of eleven naturally infested dogs in Brazil, and the inferential value to the United States population is unknown. The primary mechanism of action against C. hominivorax appears to be live larval expulsion. Additionally, the use of mechanical removal coupled with the lack of a control group confound the ability to define a pure treatment effect.

The available clinical data supporting the effectiveness of CREDELIO against C. hominivorax larvae, along with the established safety profile, support the potential benefit of CREDELIO in the authorized patient population for the treatment of infestations caused by NWS larvae.

Contraindications:

There are no known contraindications for the use of CREDELIO.

Warnings:

Not for human use. Keep this and all drugs out of the reach of children. Keep CREDELIO in a secure location out of reach of dogs, cats, and other animals to prevent accidental ingestion or overdose.

Precautions:

Lotilaner is a member of the isoxazoline class. This class has been associated with neurologic adverse reactions including tremors, ataxia, and seizures. Seizures have been reported in dogs receiving isoxazoline class drugs, even in dogs without a history of seizures. Use with caution in dogs with a history of seizures or neurologic disorders.

The safe use of CREDELIO in breeding, pregnant or lactating dogs has not been evaluated.

The safety of CREDELIO has not been evaluated in dogs less than 8 weeks of age or less than 4.4 lbs.

Adverse Reactions:

Refer to the package insert for full prescribing information, including Animal Safety, Adverse Reactions and Post-Approval Experience.

Contact Information:

To report suspected adverse events, for technical assistance or to obtain a copy of the Safety Data Sheet (SDS), contact Elanco US Inc. at 1-888-545-5973.

For additional information about adverse drug experience reporting for animal drugs, contact FDA at 1-888-FDA-VETS or http:/www.fda.gov/reportanimalae.

Information for Animal Owner:

The lifecycle for C. hominivorax is as short as 21 days and wounds can be rapidly infested. Proper wound care and management practices are essential for preventing NWS myiasis. Dogs may become reinfested following treatment.

Animal owners should be advised that:

- Gloves should be worn if cleaning the wound, or the dog’s bedding, or disposing of larvae.
- Dogs should be housed to prevent exposure to NWS flies until wounds have fully healed.
- Live larvae may exit the wound and be deposited on bedding or areas where the dog sits or lies after treatment.
- If expelled larvae are seen, owners should place the larvae in a sealed container with rubbing alcohol.
- If there is worsening of the wound, the owner should contact the veterinarian.

How Supplied:

CREDELIO is available in five chewable tablet sizes for use in dogs: 56.25, 112.5, 225, 450, and 900 mg lotilaner. Each chewable tablet size is available in color-coded packages of 1, 3 or 6 chewable tablets.

Storage Information:

Store at 15-25°C (59-77°F), excursions permitted between 5 to 40°C (41 to 104°F).

Manufactured for:
Elanco US Inc
Greenfield, IN 46140 USA

Revised October 2025

Principal Display Panel - 3 Tablets 56.25 mg Box Label

3 Tablets

Dogs &
puppies

4.4-6.0 lbs

Credelio™
(lotilaner)

For the treatment and
prevention of flea infestations
and for the treatment and control
of tick infestations in dogs and
puppies 8 weeks of age and older

56.25 mg chewable tablet

Kills fleas

Kills ticks

Monthly dose

Give with
food

CAUTION: Federal (USA) law restricts this drug to
use by or on the order of a licensed veterinarian.

Approved by FDA under NADA # 141-494

ElancoTM

Principal Display Panel - 3 Tablets 112.5 mg Box Label

3 Tablets

Dogs &
puppies

6.1-12.0 lbs

Credelio™
(lotilaner)

For the treatment and
prevention of flea infestations
and for the treatment and control
of tick infestations in dogs and
puppies 8 weeks of age and older

112.5 mg chewable tablet

Kills fleas

Kills ticks

Monthly dose

Give with
food

CAUTION: Federal (USA) law restricts this drug to
use by or on the order of a licensed veterinarian.

Approved by FDA under NADA # 141-494

ElancoTM

Principal Display Panel - 3 Tablets 225 mg Box Label

3 Tablets

Dogs &
puppies

12.1-25.0 lbs

Credelio™
(lotilaner)

For the treatment and
prevention of flea infestations
and for the treatment and control
of tick infestations in dogs and
puppies 8 weeks of age and older

225 mg chewable tablet

Kills fleas

Kills ticks

Monthly dose

Give with
food

CAUTION: Federal (USA) law restricts this drug to
use by or on the order of a licensed veterinarian.

Approved by FDA under NADA # 141-494

ElancoTM

Principal Display Panel - 3 Tablets 450 mg Box Label

3 Tablets

Dogs &
puppies

25.1-50.0 lbs

Credelio™
(lotilaner)

For the treatment and
prevention of flea infestations
and for the treatment and control
of tick infestations in dogs and
puppies 8 weeks of age and older

450 mg chewable tablet

Kills fleas

Kills ticks

Monthly dose

Give with
food

CAUTION: Federal (USA) law restricts this drug to
use by or on the order of a licensed veterinarian.

Approved by FDA under NADA # 141-494

ElancoTM

Principal Display Panel - 3 Tablets 900 mg Box Label

3 Tablets

Dogs &
puppies

50.1-100.0 lbs

Credelio™
(lotilaner)

For the treatment and
prevention of flea infestations
and for the treatment and control
of tick infestations in dogs and
puppies 8 weeks of age and older

900 mg chewable tablet

Kills fleas

Kills ticks

Monthly dose

Give with
food

CAUTION: Federal (USA) law restricts this drug to
use by or on the order of a licensed veterinarian.

Approved by FDA under NADA # 141-494

ElancoTM

Principal Display Panel – Emergency Use Authorization

For New World
screwworm (NWS)
under Emergency
Use Authorization
(EUA)

Fact Sheet

www.credelio-nws.com

EP104447A